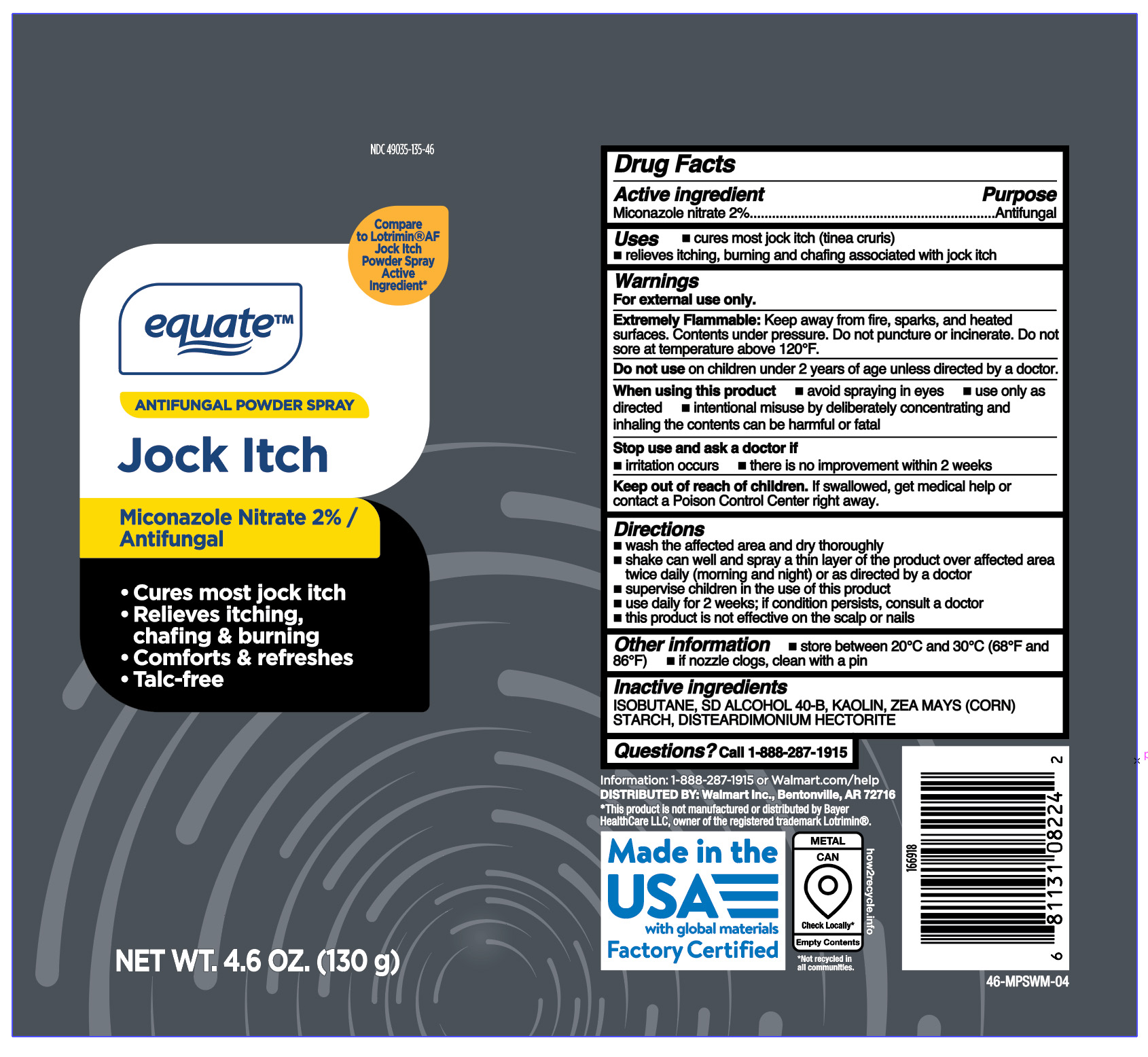 DRUG LABEL: Miconazole Nitrate
NDC: 49035-135 | Form: AEROSOL, SPRAY
Manufacturer: Wal-Mart Stores, Inc.
Category: otc | Type: HUMAN OTC DRUG LABEL
Date: 20260127

ACTIVE INGREDIENTS: MICONAZOLE NITRATE 1.3 g/130 g
INACTIVE INGREDIENTS: DISTEARDIMONIUM HECTORITE; ISOBUTANE; KAOLIN; ALCOHOL; ZEA MAYS (CORN) STARCH

Antifungal Powder Spray Jock Itch

Active ingredient

Miconazole nitrate 2%

Purpose

Antifungal

Uses

- cures most jock itch (tinea cruris)
- relieves itching, burning and chafing associated with jock itch

Warnings

For external use only.

Extremely Flammable:

Keep away from fire, sparks, and heated surfaces. Contents under pressure. Do not puncture or incinerate. Do not sore at temperature above 120°F.

Do not use

on children under 2 years of age unless directed by a doctor.

When using this product

- avoid spraying in eyes
- use only as directed
- intentional misuse by deliberately concentrating and inhaling the contents can be harmful or fatal

Stop use and ask a doctor if

- irritation occurs
- there is no improvement within 2 weeks

Keep out of reach of children.

If swallowed, get medical help or contact a Poison Control Center right away.

Directions

- wash affected area and dry thoroughly
- shake can well and spray a thin layer over affected area twice daily (morning and night) or as directed by a doctor
- supervise children in the use of this product
- use daily for 2 weeks; If conditions persists, consult a doctor
- this product is not effective on the scalp or nails

Other Information

- store between 20oC and 30oC (68o and 86oF)
- if nozzle clogs, clean with a pin

Inactive ingredient

ISOBUTANE, SD ALCOHOL 40-B, KAOLIN, ZEA MAYS (CORN) STARCH, DISTEARDIMONIUM HECTORITE

Questions?

1-888-287-1915

Principal Display Panel

equate

ANTIFUNGAL POWDER SPRAY

Jock Itch

Miconazole Nitrate 2% /

Antifungal

- Cures most jock itch
- Relieves itching,

chafing & burning

- Comforts & refreshes
- Talc-free

NET WT. 4.6 OZ. (130 g)